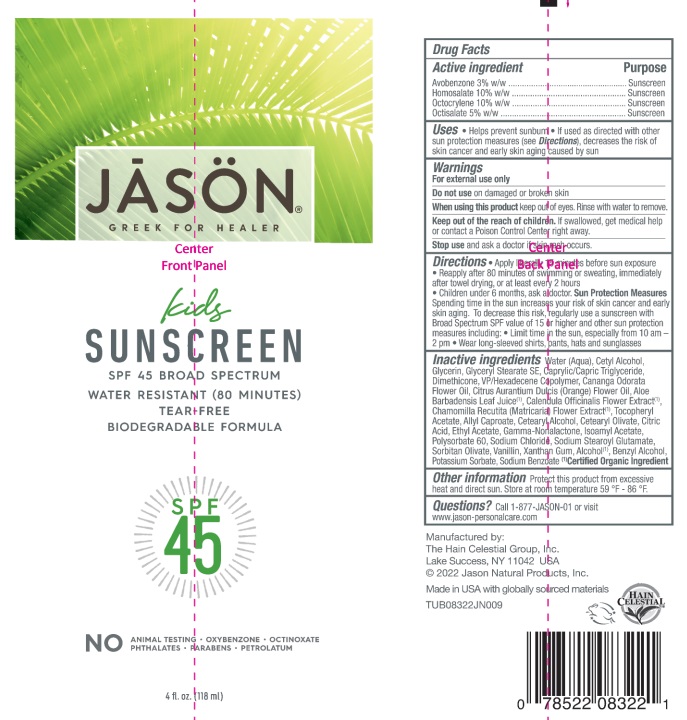 DRUG LABEL: J0832212 Jason Kids Sunscreen SPF45
NDC: 61995-0022 | Form: LOTION
Manufacturer: The Hain Celestial Group, Inc.
Category: otc | Type: HUMAN OTC DRUG LABEL
Date: 20231212

ACTIVE INGREDIENTS: AVOBENZONE 3 g/100 g; HOMOSALATE 10 g/100 g; OCTISALATE 5 g/100 g; OCTOCRYLENE 10 g/100 g
INACTIVE INGREDIENTS: .GAMMA.-NONALACTONE; ALLYL HEXANOATE; CALENDULA OFFICINALIS FLOWER; VINYLPYRROLIDONE/HEXADECENE COPOLYMER; SODIUM STEAROYL GLUTAMATE; .ALPHA.-TOCOPHEROL ACETATE; GLYCERYL STEARATE SE; POTASSIUM SORBATE; CETYL ALCOHOL; DIMETHICONE; XANTHAN GUM; CETOSTEARYL ALCOHOL; POLYSORBATE 60; MEDIUM-CHAIN TRIGLYCERIDES; CETEARYL OLIVATE; SODIUM CHLORIDE; SORBITAN OLIVATE; SODIUM BENZOATE; BENZYL ALCOHOL; CITRIC ACID MONOHYDRATE; ALOE VERA LEAF; GLYCERIN; WATER; CANANGA OIL; BENZYL BENZOATE; ORANGE OIL; ETHYL ACETATE; ISOAMYL ACETATE; VANILLIN; ALCOHOL 95%; MATRICARIA CHAMOMILLA FLOWERING TOP

J08322 Jason Kids Sunscreen SPF45
PF161505-01, 140-075C

Active Ingredient

Avobenzone - 3%

Homosalate - 10.0%

Octocrylene -10.0%

Octyl Salicylate - 5.0%

DOSAGE AND ADMINISTRATION

Apply liberally 15 minutes before sun exposure. Reapply after 80 minutes of swimming or sweating, immediately after towel drying and at least every 2 hours. Children under 6 months, ask a doctor

PURPOSE

Sunscreen

WARNINGS

For external use only. Do not use on damaged or broken skin. When using this product keep out of eyes. Rinse with water to remove. Stop use and ask a doctor if skin rash occurs.

Keep out of reach of children. If swallowed get medical help or contact Poison Center right away.

INACTIVE INGREDIENT

Water (Aqua), Cetyl Alcohol, Glycerin, Glyceryl Stearate SE, Caprylic/Capric Triglyceride, Dimethicone, VP/Hexadecene Copolymer, Cananga Odorata Flower Oil, Citrus Aurantium Dulcis (Orange) Flower Oil, Aloe Barbadensis Leaf Juice (1), Calendula Officinalis Flower Extract (1), Chamomilla Recutita (Matricaria) Flower Extract (1), Tocopheryl Acetate, Allyl Caproate, Cetearyl Alcohol, Cetearyl Olivate, Citric Acid, Ethyl Acetate, Gamma-Nonalactone, Isoamyl Acetate, Polysorbate 60, Sodium Chloride, Sodium Stearoyl Glutamate, Sorbitan Olivate, Vanillin, Xanthan Gum, Alcohol (1), Benzyl Alcohol, Potassium Sorbate, Sodium Benzoate

(1) Certified Organic Ingredient

INDICATIONS AND USAGE

Helps prevents sunburns. If used as directed with other sun protection measures, decreases risk of skin cancer and early skin aging caused by sun exposure. Skin Protection Measures: Spending time in the sun increases your risk of skin cancer and early skin aging. To decrease risk, regularly use sunscreen with Broad Spectrum SPF 15 or higher and other protective measures including: limit time in sun, especially from10am to 2pm, and wear long sleeved shirts, pants, hats and sunglases.